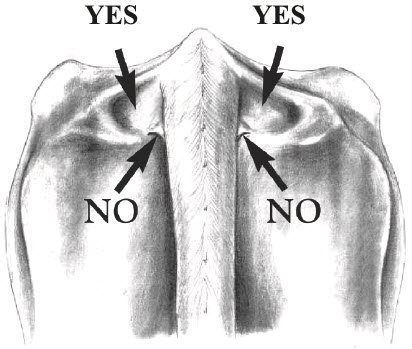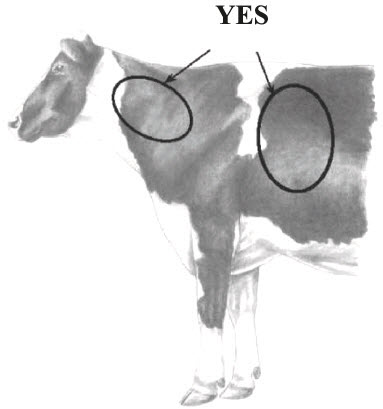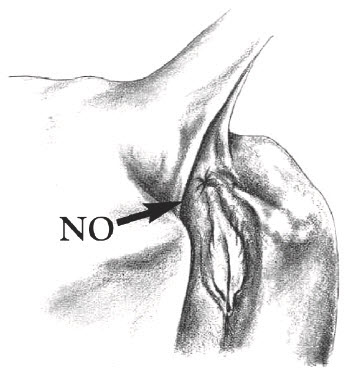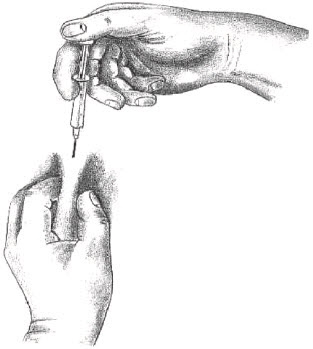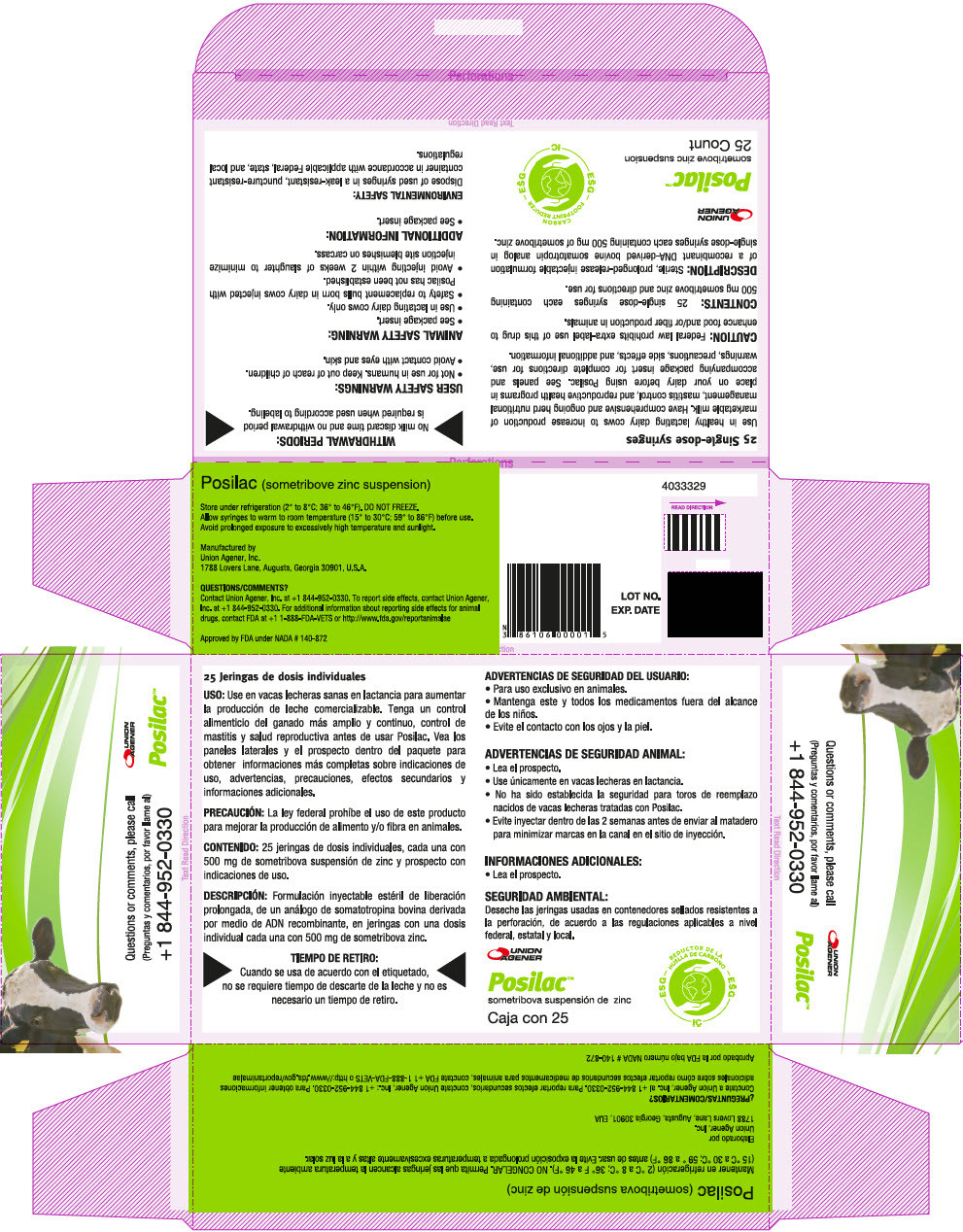 DRUG LABEL: Posilac
NDC: 86106-0225 | Form: SUSPENSION
Manufacturer: Union Agener Inc
Category: animal | Type: OTC ANIMAL DRUG LABEL
Date: 20250319

ACTIVE INGREDIENTS: sometribove 500 mg/1 1
INACTIVE INGREDIENTS: Sesame Oil; Aluminum Monostearate

Posilac™

Posilac (sometribove zinc suspension)

DESCRIPTION

DESCRIPTION: Sterile, prolonged-release injectable formulation of a recombinant DNA-derived bovine somatotropin analog in single-dose syringes each containing 500 mg of sometribove zinc.

INDICATIONS AND USAGE

USE: To increase production of marketable milk in healthy lactating dairy cows.

CAUTION: Federal law prohibits extra-label use of this drug to enhance food and/or fiber production in animals.

DOSAGE AND ADMINISTRATION

DOSAGE: Inject one syringe of Posilac every 14 days. Start during the 9th or 10th week (57-70 days) after calving and continue until the end of lactation.

DOSAGE AND ADMINISTRATION

ADMINISTRATION: Allow syringes to warm to room temperature (15° to 30° C, 59° to 86° F) before use.

INJECTION TECHNIQUE: Inject Posilac subcutaneously (under the skin). Recommended injection sites are neck area, behind the shoulder or in the depression on either side of the tailhead (see diagrams below). Alternate between the cow's left and right side on consecutive injections. Remove surface dirt from the injection site area before injecting. Inject entire contents of the syringe subcutaneously. Do not reuse syringes.

Inject directly into the deepest depressions on either side of the tailhead (marked "Yes"). Avoid the bone, muscles, tendons and ligaments of the tail and the rectal and anal muscles. Do NOT inject into the caudal fold (marked "No") because this may invalidate USDA tuberculosis testing. Locate the caudal fold by raising the tail.

INJECTION SITES:

Tailhead Depression

Neck & Behind The Shoulder

Gather skin and inject between skin and muscle layers.

WITHDRAWAL PERIODS:

No milk discard time and no withdrawal period is required when used according to labeling.

WARNINGS

USER SAFETY WARNINGS: Not for use in humans, Keep out of reach of children, Avoid prolonged or repeated contact with Posilac with eyes and skin, Posilac is a protein. Frequent skin contact with proteins may produce an allergic reaction in some people. Always wash hands and skin exposed to Posilac with soap and water after handling. Clothing soiled with the product should be laundered before reuse.

ANIMAL SAFETY WARNINGS:

- Use in lactating dairy cows only.
- Safety to replacement bulls born in dairy cows injected with Posilac has not been established.
- Avoid injecting within 2 weeks of slaughter to minimize injection site blemishes on carcass.

- Nutritional Management: Cows injected with Posilac increase voluntary feed intake over several weeks following the start of supplementation. This increase occurs sooner for first lactation cows than for second lactation or older cows. The increased feed intake continues during supplementation and may continue through the dry period and the following early lactation. However, cows treated with Posilac tend to maintain lower body condition than untreated cows. This effect is more pronounced for second lactation or older cows.

- Feed diets formulated to meet or exceed the nutritional requirements recommended by the National Research Council. Consider milk yield, stage of lactation, and body condition when making dietary changes. Manage the feeding program to optimize milk yield and to have cows in appropriate body condition, particularly during late lactation and the dry period. Increasing the energy density of diets fed to cows treated with Posilac is normaly not required. Avoid sudden dietary changes.

- Reproduction: Cows injected with Posilac may have reduced pregnancy rates and increased days open. Have a comprehensive and ongoing herd reproductive health program In place on your dairy before using Posilac.

- Mastitis: Cows injected with Posilac are at an increased risk of mastitis (visibly abnormal milk) and may have higher somatic cell counts. Have comprehensive mastitis management practices in place on your dairy before using Posilac.

- General Health: Cows injected with Posilac may require more therapeutic drug treatment for mastitis and other health problems. Cows injected with Posilac may experience periods of increased body temperature unrelated to illness. To minimize the effect, take appropriate measures during periods of high environmental temperature to reduce heat stress. Use care to differentiate whether increased body temperature is caused by illness or use of Posilac. Cows injected with Posilac may have more enlarged hocks and disorders of the foot region. Posilac treatment may reduce hemoglobin and hematocrit values.

- Injection Site Reactions: A mild temporary swelling of 3-5 cm (1-2 inches) in diameter may occur at the injection site beginning about 3 days after injection and may persist up to 6 weeks following injection. Larger swellings may occur in cows injected in the neck area compared to the behind the shoulder or in the depression on either side of the tailhead. Some cows may experience swellings up to 10 cm (4 inches) in diameter that remain permanent but are not associated with animal health problems. However, if permanent blemishes are objectionable to you, stop supplementation of these cows. Also stop using Posilac in cows with injection site swellings that repeatedly open and drain.

- Udder Edema: Posilac is approved for use starting during the 9th or 10th week of lactation. Risk of udder edema may increase if injections start later in lactation.

ADDITIONAL INFORMATION:

- Milk production response during each 14-day injection period is cyclic and will be greatest during the middle of each period.

STORAGE AND HANDLING

STORAGE: Store under refrigeration (2° to 8° C; 36° to 46° F). DO NOT FREEZE. Allow syringes to warm to room temperature (15° to 30° C; 59° to 86° F) before use. Avoid prolonged exposure to excessively high temperature and sunlight. Expiration dates are stated on syringes and box labeling.

ENVIRONMENTAL WARNING

ENVIRONMENTAL SAFETY: Dispose of used syringes in a leak-resistant, puncture-resistant container in accordance with applicable Federal, state, and local regulations.

HOW SUPPLIED

HOW SUPPLIED: Single-dose syringes in 25 or 100 count boxes.

QUESTIONS/COMMENTS?

Contact Union Agener, Inc. at +1 844-952-0330. To report side effects, contact Union Agener, Inc. at +1 844-952-0330. For additional information about reporting side effects for animal drugs, contact FDA at + 1 1-888-FDA-VETS or http://www.fda.gov/reportanimalae

Approved by FDA under NADA # 140-872
Manufactured by
Union Agener, Inc.
1788 Lovers Lane, Augusta, Georgia 30901, U.S.A.
4024774

PRINCIPAL DISPLAY PANEL - 25 Syringe Carton

Posilac (sometribove zinc suspension)

Store under refrigeration (2° to 8°C; 36° to 46°F). DO NOT FREEZE.
Allow syringes to warm to room temperature (15° to 30°C; 59° to 86°F before use.
Avoid prolonged exposure to excessively high temperature and sunlight.

Manufactured by
Union Agener, Inc.
1788 Lovers Lane, Augusta, Georgia 30901, U.S.A.

QUESTIONS/COMMENTS?

Contact Union Agener, Inc. at +1 844-952-0330. To report side effects, contact Union Agener,
Inc. at +1 844-952-0330. For additional information about reporting side effects for animal
drugs, contact FDA at +1 1-888-FDA-VETS or http://www.fda.gov/reportanimalae

Approved by FDA under NADA # 140-872